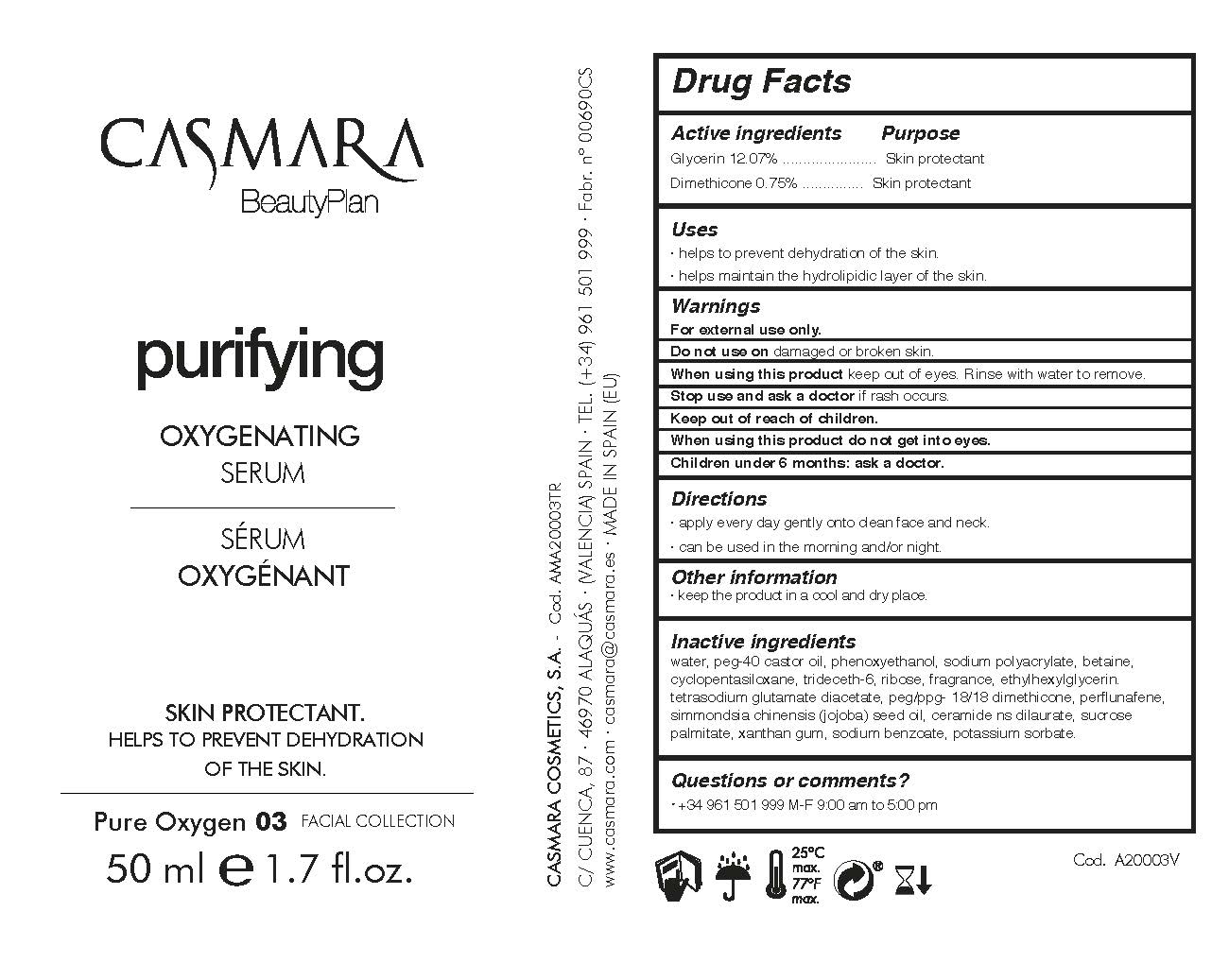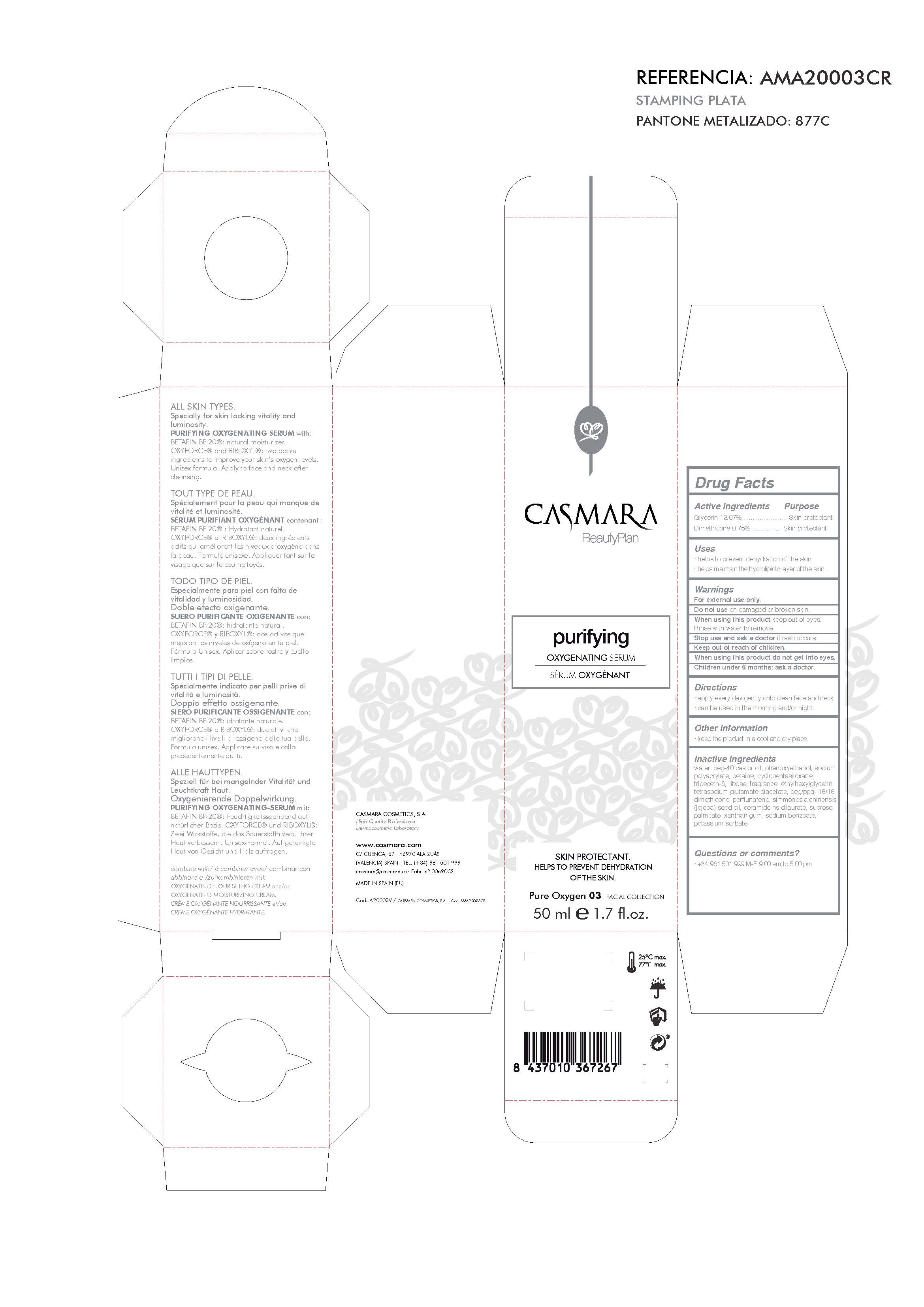 DRUG LABEL: Purifying Oxygenating Serum
NDC: 20151-056 | Form: CREAM
Manufacturer: Casmara Cosmetics, SA
Category: otc | Type: HUMAN OTC DRUG LABEL
Date: 20161125

ACTIVE INGREDIENTS: DIMETHICONE 0.75 mg/1 mL; GLYCERIN 12 mg/1 mL
INACTIVE INGREDIENTS: ETHYLHEXYLGLYCERIN 0.1 mg/1 mL; WATER 81.874 mg/1 mL; CERAMIDE NS DILAURATE 0.0006 mg/1 mL; SUCROSE PALMITATE 0.006 mg/1 mL; XANTHAN GUM 0.001 mg/1 mL; PEG-40 CASTOR OIL 2 mg/1 mL; PHENOXYETHANOL 0.9 mg/1 mL; SODIUM POLYACRYLATE (8000 MW) 0.75 mg/1 mL; BETAINE 0.5 mg/1 mL; DIMETHICONE CROSSPOLYMER (450000 MPA.S AT 12% IN CYCLOPENTASILOXANE) 0.22 mg/1 mL; TRIDECETH-6 0.22 mg/1 mL; RIBOSE, D- 0.2 mg/1 mL; TETRASODIUM GLUTAMATE DIACETATE 0.096 mg/1 mL; PEG/PPG-18/18 DIMETHICONE 0.09 mg/1 mL; PERFLUNAFENE 0.035 mg/1 mL; SIMMONDSIA CHINENSIS SEED 0.015 mg/1 mL; SODIUM BENZOATE 0.001 mg/1 mL; POTASSIUM SORBATE 0.001 mg/1 mL

Purifying Oxygenating Serum

ACTIVE INGREDIENTS PURPOSE

Glycerin 6.5%............. Skin Protectant

Dimethicone 0.75%.....Skin Protectant

USES

. helps to prevent dehydration of the skin.

- helps maintain the hydrolipidic layer of the skin.

USES

. helps to prevent the dehydration of the skin

. helps maintain the hydrolipidic layer of the skin

Warnings

For external use only.

Do not use on damaged or broken skin.

When using this product keep our of the eyes. Rinse with water to remove.

Stop use and ask a doctor if rash occurs.

Keep out of reach of children.

Whhen using this product do not get into eyes.

Children under 6 months: as a doctor.

WARNINGS

Stop use and ask a doctor if rash occurs

Children under 6 months: ask a doctor

Warnings

Keep out of reach of children

Questions or comments?

+ 34 961 501 999 M-F 9:00 am to 5:00 pm

Other Information

. keep the product in a cool and dry place

Directions

. apply every day gently onto clean face and neck

. can be used in the morning and/or night

DOSAGE AND ADMINISTRATION

. apply every day gently onto clean dace and neck

. can be used in the morning and/or night

INACTIVE INGREDIENTS

Water, PEG-40 Castor oil, phenoxyethanol, sodium polyacrylate, betaine, cyclopentasiloxane, trideceth-6, ribose, fragrance, ethylhexylglycerin, tetrasodium glutamate diacetate, PEG/PPG- 18/18 dimethicone, perfluorodecalin, simmondsia chinensis (jojoba) seed oil, ceramide np, sucrose palmitate, xanthan gum, sodium benzoate, potassium sorbate

Purifying Oxygenating Serum See below image

Skin Protectant

Helps to Prevent Dehydration of the Skin

Pure Ocygen 03 Facial Collection

50 ml 1.7 fl.oz.

Package Label

Please see image below. Package Label